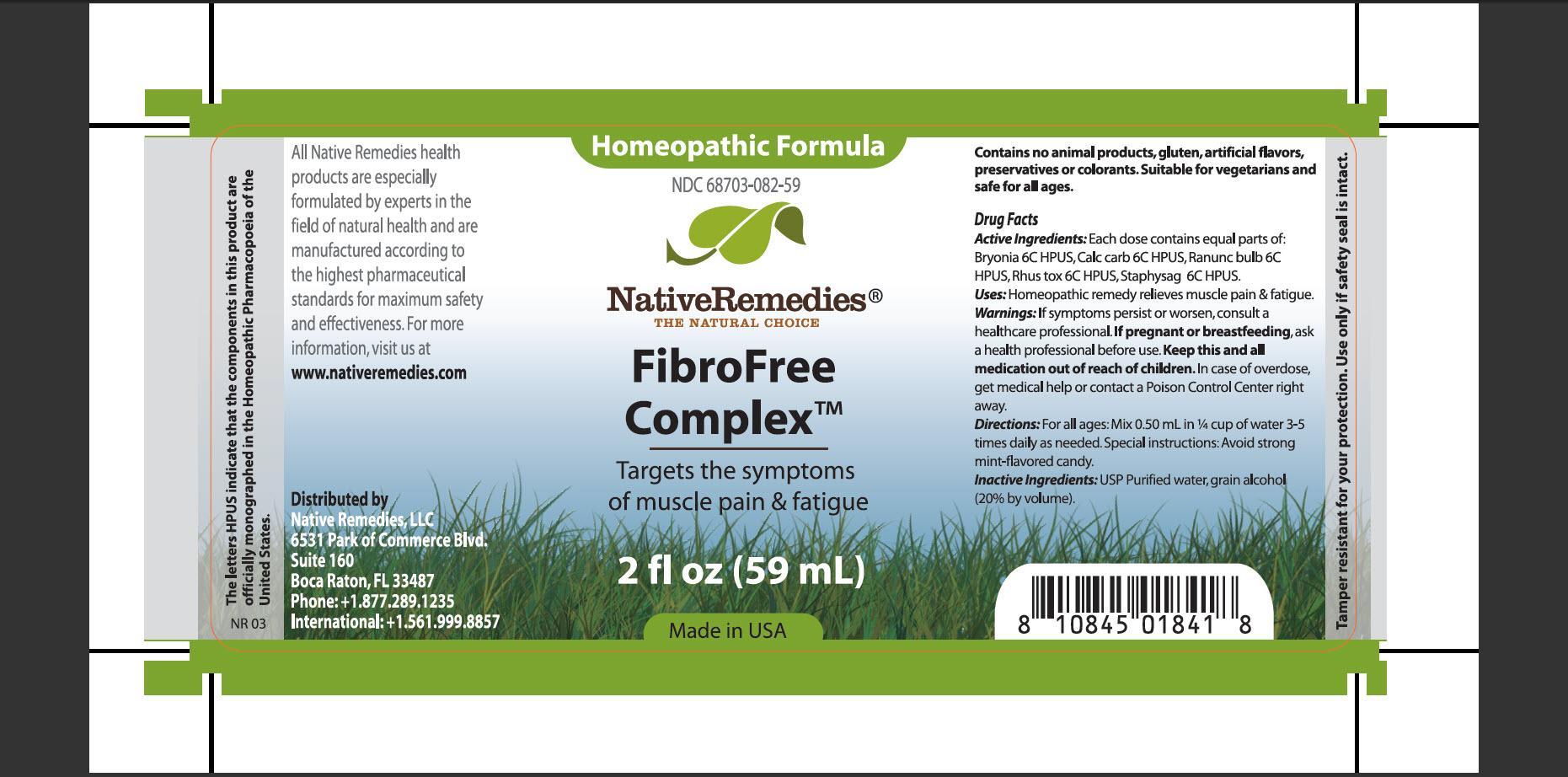 DRUG LABEL: FibroFree Complex
NDC: 68703-082 | Form: TINCTURE
Manufacturer: Native Remedies, LLC
Category: homeopathic | Type: HUMAN OTC DRUG LABEL
Date: 20130425

ACTIVE INGREDIENTS: BRYONIA ALBA ROOT 6 [hp_C]/1 mL; OYSTER SHELL CALCIUM CARBONATE, CRUDE 6 [hp_C]/1 mL; RANUNCULUS BULBOSUS 6 [hp_C]/1 mL; TOXICODENDRON PUBESCENS LEAF  6 [hp_C]/1 mL; DELPHINIUM STAPHISAGRIA SEED 6 [hp_C]/1 mL
INACTIVE INGREDIENTS: WATER; ALCOHOL

FibroFree Complex

PURPOSE

Targets the symptoms of muscle pain and fatigue

ACTIVE INGREDIENT

Active Ingredients: Each dose contains equal parts of: Bryonia 6C HPUS, Calc carb 6C HPUS, Ranunc bulb 6C HPUS, Rhus tox 6C HPUS, Staphysag 6C HPUS

INDICATIONS AND USAGE

Uses: Homeopathic remedy relieves muscle pain and fatigue

WARNINGS

Warnings: If symptoms persist or worsen, consult a healthcare professional

PREGNANCY OR BREAST FEEDING

If pregnant or breastfeeding, ask a health professional before use

KEEP OUT OF REACH OF CHILDREN

Keep this and all medication out of reach of children

OVERDOSAGE

In case of overdose, get medical help or contact a Poison Control Center right away

DOSAGE AND ADMINISTRATION

Directions: For all ages: Mix 0.50 mL in 1/4 cup of water 3-5 times daily as needed. Special instructions: Avoid strong mint-flavored candy

INACTIVE INGREDIENT

Inactive Ingredients: USP Purified water, grain alcohol (20% by volume)

PATIENT COUNSELING INFORMATION

The letters HPUS indicate that the components in this product are officially monographed in the Homeopathic Pharmacopoeia of the United States

All Native Remedies health products are especially formulated by experts in the field of natural health and are manufactured according to the highest pharmaceutical standards for maximum safety and effectiveness. For more information, visit us at www.nativeremedies.com

Distributed by
Native Remedies, LLC
6531 Park of Commerce Blvd.
Suite 160
Boca Raton, FL 33487
Phone: +1.877.289.1235
International: +1.561.999.8857

Contains no animal products, gluten, artificial flavors, preservatives or colorants. Suitable for vegetarians and safe for all ages

STORAGE AND HANDLING

Tamper resistant for your protection. Use only if safety seal is intact